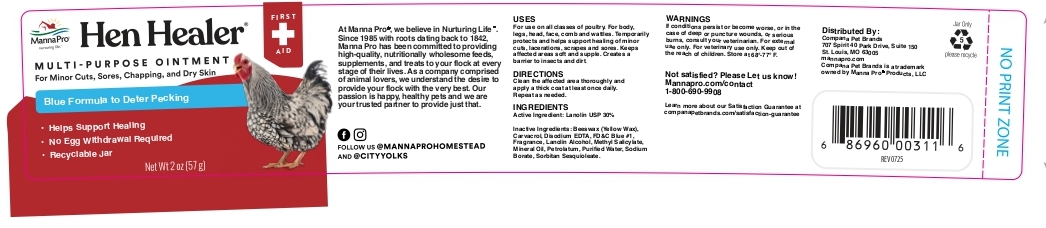 DRUG LABEL: Hen Healer Multi-Purpose
NDC: 86077-3001 | Form: Ointment
Manufacturer: Manna Pro Products LLC
Category: animal | Type: OTC ANIMAL DRUG LABEL
Date: 20250818

ACTIVE INGREDIENTS: LANOLIN 30 g/100 g
INACTIVE INGREDIENTS: SORBITAN SESQUIOLEATE

Hen Healer Multi-Purpose Ointment

Drug Facts

Active Ingredient: Lanolin 30%

Purpose: Skin Protectant

USES

For use on all classses of poultry. For body, legs, head, face, comb and wattles. Temporarily protects and helps support healing of minor cuts, lacerations, scrapes and sores. Keeps affected areas soft and supple. Creates a barrier to insisects and dirt.

WARNINGS:

If conditions persist or become worse, or in the case of deep or puncture wounds, or serious burns, consult your veterinarian.

Keep out of the reach of children.

DIRECTIONS

Clean the affected area thoroughly and apply a thick coat at least once daily. Repeat as needed.

OTHER INFORMATION

Store at 68-77 degrees F.

Inactive Ingredients

Beeswax (Yellow Wax), Carvacrol, Disodium EDTA, FD&C Blue #1, Fragrance, Lanolin Alcohol, Methyl Salicylate, Mineral Oil, Petrolatum, Purified Water, Sodium Borate, Sorbitan Sesquioleate.

QUESTIONS

Not satisfied? Please Let us knoe!

Mannapro.com/contact

1-800-690-9908

PACKAGE LABEL

Hen Healer MULTI-PURPOSE OINTMENT

For Minor Cuts, Sores, Chapping, and Dry Skin

Blue Formula to Deter Pecking

- Helps Support Healing

- No Egg Withdrawal Required

- Recyclable Jar

At Manna Pro, we believe in Nurturing Life. Since 1985 with roots dating back to 1842, Manna Pro has been committed to providing high-quality, nutritionally wholesome feeds, supplements, and treats to your flock at every stage of their lives. As a company comprised of animal lovers, we understand the desire to provide your flock with the very best. Our passion is happy, healthy pets and we are your trusted partner to provide just that.

Distributed By:

Compana Pet Brands

7078 Spirit 40 Park Drive, SUite 150

St. Louis, MO 63005

mannapro.com

Compana Pet Brands is a trademark

pwned by Manna Pro Products, LLC